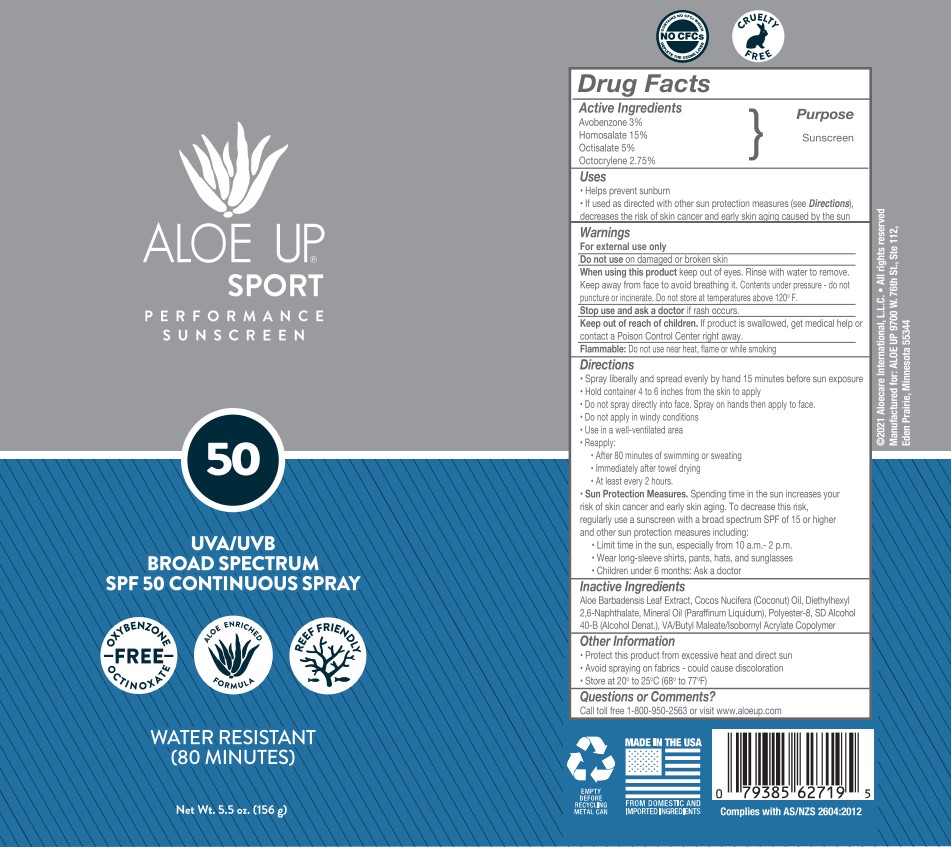 DRUG LABEL: The Venetian The Palazzo
NDC: 13630-0256 | Form: SPRAY
Manufacturer: Prime Packaging Inc.
Category: otc | Type: HUMAN OTC DRUG LABEL
Date: 20221108

ACTIVE INGREDIENTS: OCTOCRYLENE 23.07 g/1 mL; AVOBENZONE 25.17 g/1 mL; OCTISALATE 41.95 g/1 mL; HOMOSALATE 125.85 g/1 mL
INACTIVE INGREDIENTS: DIETHYLHEXYL 2,6-NAPHTHALATE; MINERAL OIL; POLYESTER-8 (1400 MW, CYANODIPHENYLPROPENOYL CAPPED); ALCOHOL; COCONUT OIL; ALOE VERA LEAF

The venetian The palazzo Broad Spectrum SPF 50 Sport Sunscreen Spray

Active Ingredients

Avobenzone 3%

Homosalate 15%

Octisalate 5%

Octocrylene 2.75%

Purpose

Sunscreen

Uses

- Helps prevent sunburn
  - If used as directed with other sun protection measures (see Directions) decreases the risk of skin cancer and early skin aging caused by the sun

Warnings

For external use only

Do not use on damaged or broken skin

When using this product keep out of eyes. Rinse with water to remove. Keep away from face to avoid breathing it. Contents under pressure - do not puncture or incinerate. Do not store at temperatures above 120º F.

Stop use and ask a doctor if rash occurs.

Keep out of reach of children. If product is swallowed, get medical help or contact a Poison Control Center right away.

Flammable: Do not use near heat, flame or while smoking

Directions

- Spray liberally and spread evenly 15 minutes before sun exposure
- Hold container 4 to 6 inches from the skin to apply
- Do not spray directly into face. Spray on hands then apply to face.
- Do not apply in windy conditions
- Use in well-ventilated area
- Reapply:
- After 80 minutes of swimming or sweating
- Immediately after towel drying
- At least every 2 hours.
- Sun Protection Measures Spending time in the sun increases your risk of skin cancer and early skin aging. To decrease this risk, regularly use a sunscreen with a broad spectrum SPF of 15 or higher and other sun protecion measures including:
- Limit time in the sun, especially from 10 a.m. - 2 p.m.
- Wear long sleeve shirts, pants, hats, and sunglasses
- Children under 6 months: Ask a doctor

INACTIVE INGREDIENTS

Aloe Barbadensis Leaf Extract, Cocos Nucifera (Coconut) Oil, Diethylhexyl 2,6-Naphthalate, Mineral Oil, Polyester-8, SD Alcohol 40-B, VA/Butyl Maleate/Isobornyl Acrylate Copolymer

Other Information

- Protect this product from excessive heat and direct sun
- Avoid spraying on fabrics - could cause discoloration
- Store at 20° to 25°C (68° to 77°F)

Questions or Comments?

Call toll free 1-800-950-2563 or visit www.aloeup.com